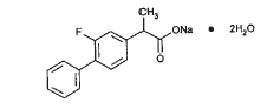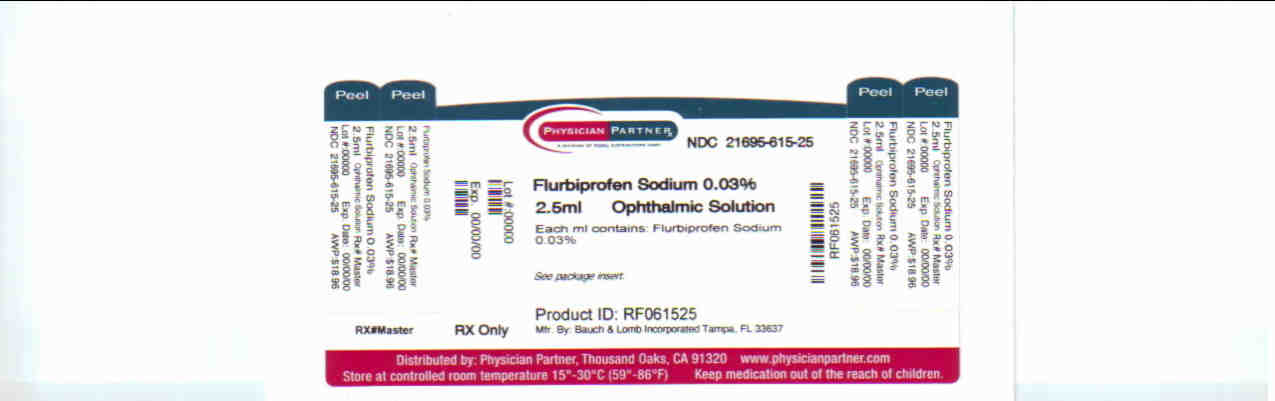 DRUG LABEL: Flurbiprofen Sodium
NDC: 21695-615 | Form: SOLUTION/ DROPS
Manufacturer: Rebel Distributors Corp
Category: prescription | Type: HUMAN PRESCRIPTION DRUG LABEL
Date: 20100928

ACTIVE INGREDIENTS: Flurbiprofen Sodium 0.242 mg/1 mL
INACTIVE INGREDIENTS: Citric Acid; Edetate Disodium; Hydrochloric Acid; POLYVINYL ALCOHOL; Potassium Chloride; Water; Sodium Chloride; Sodium Citrate; Sodium Hydroxide; Thimerosal

Flurbiprofen Sodium Ophthalmic Solution USP, 0.03%

DESCRIPTION

Flurbiprofen Sodium Ophthalmic Solution USP, 0.03% is a sterile topical nonsteroidal anti-inflammatory product for ophthalmic use. Flurbiprofen sodium is represented by the following structural formula:

C15H12 FNaO2 •2H2O

Mol. Wt. 302.27

Chemical Name: Sodium (±)-2-(2-fluoro-4-biphenyl)-propionate dihydrate.

Each mL Contains: ACTIVE: Flurbiprofen sodium 0.03%;

INACTIVES: Sodium Citrate, Polyvinyl Alcohol 1.4%, Edetate Disodium, Potassium Chloride, Sodium Chloride, Citric Acid, Purified Water. Hydrochloric Acid and/or Sodium Hydroxide may be added to adjust pH (6.0 – 7.0).

PRESERVATIVE ADDED: Thimerosal 0.005%.

CLINICAL PHARMACOLOGY

Flurbiprofen sodium is one of a series of phenylalkanoic acids that have shown analgesic antipyretic, and antiinflammatory activity in animal inflammatory diseases. Its mechanism of action is believed to be through inhibition of the cyclo-oxygenase enzyme that is essential in the biosynthesis of prostaglandins.

Prostaglandins have been shown in many animal models to be mediators of certain kinds of intraocular inflammation. In studies performed on animal eyes, prostaglandins have been shown to produce disruption of the blood-aqueous humor barrier, vasodilatation, increased vascular permeability, leukocytosis, and increased intraocular pressure.

Prostaglandins also appear to play a role in the miotic response produced during ocular surgery by constricting the iris sphincter independently of cholinergic mechanisms. In clinical studies, flurbiprofen sodium ophthalmic solution has been shown to inhibit the miosis induced during the course of cataract surgery.

Results from clinical studies indicate that flurbiprofen sodium has no significant effect upon intraocular pressure.

INDICATIONS AND USAGE

Flurbiprofen sodium ophthalmic solution is indicated for the inhibition of intraoperative miosis.

CONTRAINDICATIONS

Flurbiprofen sodium ophthalmic solution is contraindicated in individuals who are hypersensitive to any components of the medication.

WARNINGS

With nonsteroidal anti-inflammatory drugs, there exists the potential for increased bleeding due to interference with thrombocyte aggregation. There have been reports that flurbiprofen sodium ophthalmic solution may cause increased bleeding of ocular tissues in conjunction with ocular surgery.

There exists the potential for cross-sensitivity to acetylsalicylic acid and other nonsteroidal anti-inflammatory drugs. Therefore, caution should be used when treating individuals who have previously exhibited sensitivities to these drugs.

PRECAUTIONS

General

Wound healing may be delayed with the use of flurbiprofen sodium ophthalmic solution.

It is recommended that flurbiprofen sodium ophthalmic solution be used with caution in surgical patients with known bleeding tendencies or who are receiving other medications which may prolong bleeding time.

Drug Interactions

Interaction of flurbiprofen sodium ophthalmic solution with other topical ophthalmic medications has not been fully investigated.

Although clinical studies with acetylcholine chloride and animal studies with acetylcholine chloride or carbachol revealed no interference, and there is no known pharmacological basis for an interaction, there have been reports that acetylcholine chloride and carbachol have been ineffective when used in patients treated with flurbiprofen sodium ophthalmic solution.

Carcinogenesis, mutagenesis, impairment of fertility

Long-term studies in mice and/or rats have shown no evidence of carcinogenicity or impairment of fertility with flurbiprofen.

Long-term mutagenicity studies in animals have not been performed.

Pregnancy

Pregnancy Category C. Flurbiprofen has been shown to be embryocidal, delay parturition, prolong gestation, reduce weight, and/or slightly retard growth of fetuses when given to rats in daily oral doses of 0.4 mg/kg (approximately 67 times the human daily topical dose) and above. There are no adequate and well-controlled studies in pregnant women. Flurbiprofen sodium ophthalmic solution should be used during pregnancy only if the potential benefit justifies the potential risk to the fetus.

Nursing mothers

It is not known whether this drug is excreted in human milk. Because many drugs are excreted in human milk and because of the potential for serious adverse reactions in nursing infants from flurbiprofen sodium, a decision should be made whether to discontinue nursing or to discontinue the drug, taking into account the importance of the drug to the mother.

Pediatric use

Safety and effectiveness in pediatric patients have not been established.

Geriatric use

No overall differences in safety or effectiveness have been observed between elderly and younger patients

ADVERSE REACTIONS

Transient burning and stinging upon instillation and other minor symptoms of ocular irritation have been reported with the use of flurbiprofen sodium ophthalmic solution. Other adverse reactions reported with the use of flurbiprofen sodium ophthalmic solution include: fibrosis, miosis, and mydriasis.

Increased bleeding tendency of ocular tissues in conjunction with ocular surgery has also been reported.

Overdosage

Overdosage will not ordinarily cause acute problems. If accidentally ingested, drink fluids to dilute.

DOSAGE AND ADMINISTRATION

A total of four (4) drops of flurbiprofen sodium ophthalmic solution should be administered by instilling 1 drop approximately every 1/2 hour beginning 2 hours before surgery.

HOW SUPPLIED

Flurbiprofen Sodium Ophthalmic Solution USP, 0.03% is supplied in a plastic bottle with a controlled drop tip in the following size:

2.5 mL - Prod. No. 31404

DO NOT USE IF IMPRINTED “Protective Seal” WITH YELLOW IS NOT INTACT.

Storage

Store between 15°–30°C (59°–86°F).

Rx only

FOR OPHTHALMIC USE ONLY

Manufacturer Information

Bausch & Lomb Incorporated

Tampa, Florida 33637

©Bausch & Lomb Incorporated

Repackaged by:

Rebel Distributors Corp

Thousand Oaks, CA 91320